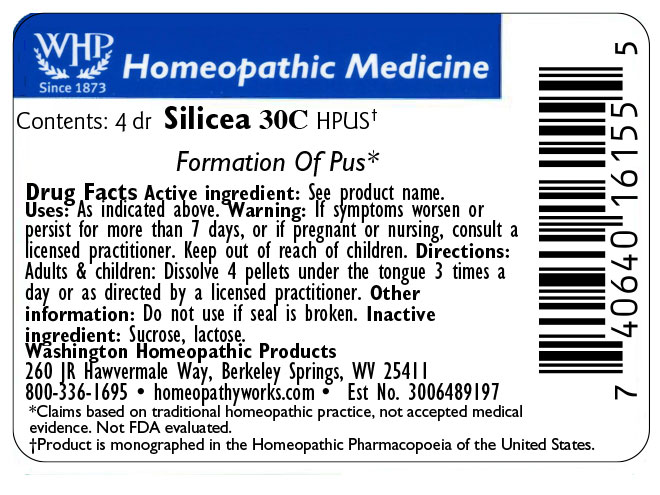 DRUG LABEL: Silicea
NDC: 71919-827 | Form: PELLET
Manufacturer: Washington Homeopathic Products
Category: homeopathic | Type: HUMAN OTC DRUG LABEL
Date: 20250224

ACTIVE INGREDIENTS: SILICON DIOXIDE 30 [hp_C]/1 1
INACTIVE INGREDIENTS: SUCROSE; LACTOSE

Silicea 4dram

ACTIVE INGREDIENT

SILICON DIOXIDE

PURPOSE

Indicated for Formation of pus

KEEP OUT OF REACH OF CHILDREN

As with all medicines, keep out of reach of children.

INDICATIONS AND USAGE

SILICEA Formation of pus

WARNINGS

If symptoms worsen or persist for more than 7 days, or if pregnant or nursing, consult a licensed practitioner.

DOSAGE AND ADMINISTRATION

Directions: Adults & children: Dissolve 4 pellets under the tongue 3 times a day or as directed by a licensed practitioner. Other information: Do not use if seal is broken.

INACTIVE INGREDIENT

SUCROSE/LACTOSE

PACKAGE LABEL

The OTC potency range of Silicea is 30c - 200c.

Availability is subject to change.